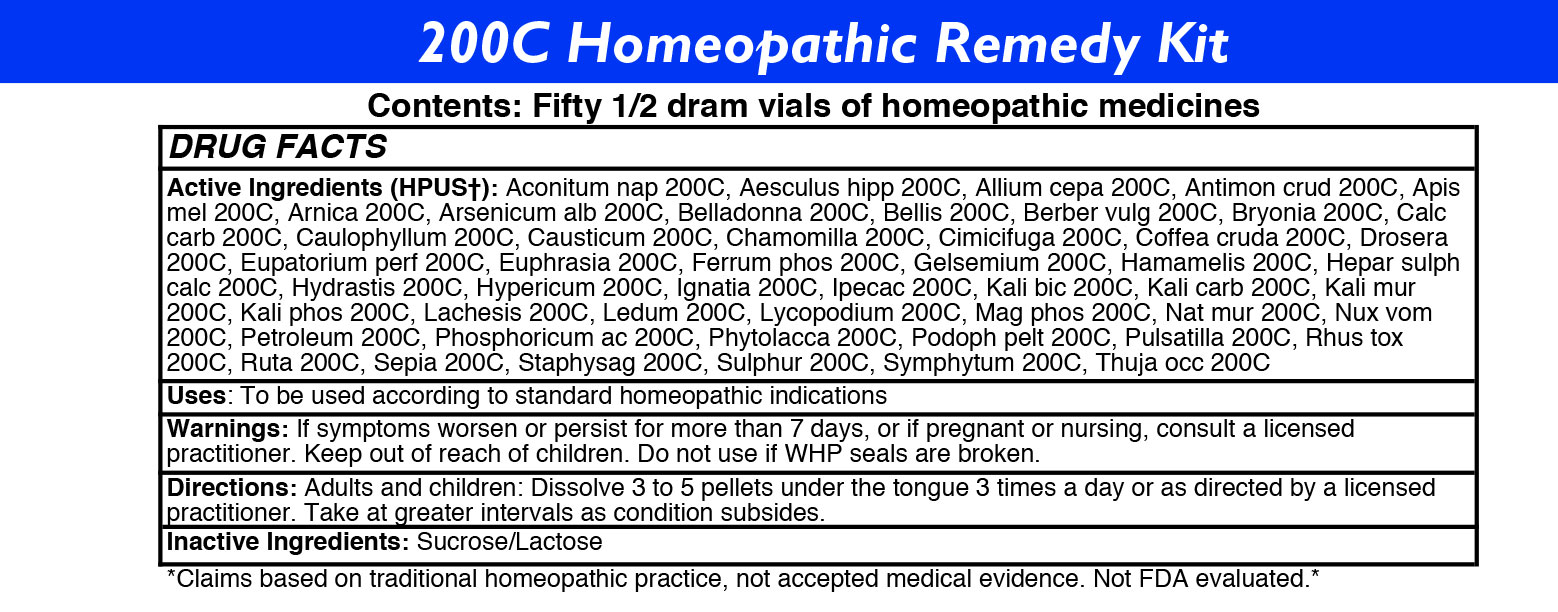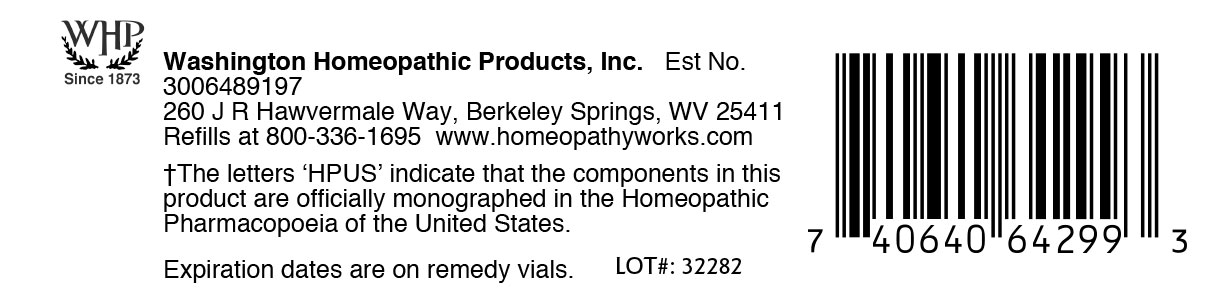 DRUG LABEL: 200C Homeopathic Remedy Kit
NDC: 71919-822 | Form: KIT | Route: ORAL
Manufacturer: Washington Homeopathic Products
Category: homeopathic | Type: HUMAN OTC DRUG LABEL
Date: 20260108

ACTIVE INGREDIENTS: ACONITUM NAPELLUS 200 [hp_C]/1 1; HORSE CHESTNUT 200 [hp_C]/1 1; ONION 200 [hp_C]/1 1; ANTIMONY TRISULFIDE 200 [hp_C]/1 1; APIS MELLIFERA 200 [hp_C]/1 1; ARNICA MONTANA 200 [hp_C]/1 1; ARSENIC TRIOXIDE 200 [hp_C]/1 1; ATROPA BELLADONNA 200 [hp_C]/1 1; BELLIS PERENNIS 200 [hp_C]/1 1; BERBERIS VULGARIS ROOT BARK 200 [hp_C]/1 1; BRYONIA ALBA ROOT 200 [hp_C]/1 1; OYSTER SHELL CALCIUM CARBONATE, CRUDE 200 [hp_C]/1 1; CAULOPHYLLUM THALICTROIDES ROOT 200 [hp_C]/1 1; CAUSTICUM 200 [hp_C]/1 1; MATRICARIA RECUTITA 200 [hp_C]/1 1; BLACK COHOSH 200 [hp_C]/1 1; ARABICA COFFEE BEAN 200 [hp_C]/1 1; DROSERA ROTUNDIFOLIA FLOWERING TOP 200 [hp_C]/1 1; EUPATORIUM PERFOLIATUM FLOWERING TOP 200 [hp_C]/1 1; EUPHRASIA STRICTA 200 [hp_C]/1 1; FERROSOFERRIC PHOSPHATE 200 [hp_C]/1 1; GELSEMIUM SEMPERVIRENS ROOT 200 [hp_C]/1 1; HAMAMELIS VIRGINIANA ROOT BARK/STEM BARK 200 [hp_C]/1 1; CALCIUM SULFIDE 200 [hp_C]/1 1; GOLDENSEAL 200 [hp_C]/1 1; HYPERICUM PERFORATUM 200 [hp_C]/1 1; STRYCHNOS IGNATII SEED 200 [hp_C]/1 1; IPECAC 200 [hp_C]/1 1; POTASSIUM DICHROMATE 200 [hp_C]/1 1; POTASSIUM CARBONATE 200 [hp_C]/1 1; POTASSIUM CHLORIDE 200 [hp_C]/1 1; POTASSIUM PHOSPHATE, DIBASIC 200 [hp_C]/1 1; LACHESIS MUTA VENOM 200 [hp_C]/1 1; LEDUM PALUSTRE TWIG 200 [hp_C]/1 1; LYCOPODIUM CLAVATUM SPORE 200 [hp_C]/1 1; MAGNESIUM PHOSPHATE, DIBASIC TRIHYDRATE 200 [hp_C]/1 1; SODIUM CHLORIDE 200 [hp_C]/1 1; STRYCHNOS NUX-VOMICA SEED 200 [hp_C]/1 1; KEROSENE 200 [hp_C]/1 1; PHOSPHORIC ACID 200 [hp_C]/1 1; PHYTOLACCA AMERICANA ROOT 200 [hp_C]/1 1; PODOPHYLLUM PELTATUM ROOT 200 [hp_C]/1 1; PULSATILLA VULGARIS 200 [hp_C]/1 1; TOXICODENDRON RADICANS LEAF 200 [hp_C]/1 1; RUTA GRAVEOLENS FLOWERING TOP 200 [hp_C]/1 1; SEPIA OFFICINALIS JUICE 200 [hp_C]/1 1; DELPHINIUM STAPHISAGRIA SEED 200 [hp_C]/1 1; SULFUR 200 [hp_C]/1 1; COMFREY ROOT 200 [hp_C]/1 1; THUJA OCCIDENTALIS LEAFY TWIG 200 [hp_C]/1 1
INACTIVE INGREDIENTS: SUCROSE; LACTOSE, UNSPECIFIED FORM; SUCROSE; LACTOSE, UNSPECIFIED FORM; SUCROSE; LACTOSE, UNSPECIFIED FORM; LACTOSE, UNSPECIFIED FORM; SUCROSE; LACTOSE, UNSPECIFIED FORM; SUCROSE; LACTOSE, UNSPECIFIED FORM; SUCROSE; LACTOSE, UNSPECIFIED FORM; SUCROSE; LACTOSE, UNSPECIFIED FORM; SUCROSE; LACTOSE, UNSPECIFIED FORM; SUCROSE; LACTOSE, UNSPECIFIED FORM; SUCROSE; LACTOSE, UNSPECIFIED FORM; SUCROSE; LACTOSE, UNSPECIFIED FORM; SUCROSE; SUCROSE; LACTOSE, UNSPECIFIED FORM; SUCROSE; LACTOSE, UNSPECIFIED FORM; LACTOSE, UNSPECIFIED FORM; SUCROSE; SUCROSE; LACTOSE, UNSPECIFIED FORM; LACTOSE, UNSPECIFIED FORM; SUCROSE; LACTOSE, UNSPECIFIED FORM; SUCROSE; SUCROSE; LACTOSE, UNSPECIFIED FORM; SUCROSE; LACTOSE, UNSPECIFIED FORM; LACTOSE, UNSPECIFIED FORM; SUCROSE; LACTOSE, UNSPECIFIED FORM; SUCROSE; SUCROSE; LACTOSE, UNSPECIFIED FORM; SUCROSE; LACTOSE, UNSPECIFIED FORM; LACTOSE, UNSPECIFIED FORM; SUCROSE; LACTOSE, UNSPECIFIED FORM; SUCROSE; SUCROSE; LACTOSE, UNSPECIFIED FORM; LACTOSE, UNSPECIFIED FORM; SUCROSE; SUCROSE; LACTOSE, UNSPECIFIED FORM; SUCROSE; LACTOSE, UNSPECIFIED FORM; LACTOSE, UNSPECIFIED FORM; SUCROSE; SUCROSE; LACTOSE, UNSPECIFIED FORM; LACTOSE, UNSPECIFIED FORM; SUCROSE; LACTOSE, UNSPECIFIED FORM; SUCROSE; LACTOSE, UNSPECIFIED FORM; SUCROSE; SUCROSE; LACTOSE, UNSPECIFIED FORM; SUCROSE; LACTOSE, UNSPECIFIED FORM; LACTOSE, UNSPECIFIED FORM; SUCROSE; LACTOSE, UNSPECIFIED FORM; SUCROSE; SUCROSE; LACTOSE, UNSPECIFIED FORM; SUCROSE; LACTOSE, UNSPECIFIED FORM; LACTOSE, UNSPECIFIED FORM; SUCROSE; SUCROSE; LACTOSE, UNSPECIFIED FORM; LACTOSE, UNSPECIFIED FORM; SUCROSE; LACTOSE, UNSPECIFIED FORM; SUCROSE; LACTOSE, UNSPECIFIED FORM; SUCROSE; LACTOSE, UNSPECIFIED FORM; SUCROSE; LACTOSE, UNSPECIFIED FORM; SUCROSE; SUCROSE; LACTOSE, UNSPECIFIED FORM; LACTOSE, UNSPECIFIED FORM; SUCROSE

WHP 200C Homeopathic Remedy Kit

ACTIVE INGREDIENTS

Acon nap
Aesculus hipp
Allium cepa
Antimon crud
Apis mel
Arnica
Arsenicum alb
Belladonna
Bellis
Berber vulg
Bryonia
Calc carb
Caulophyllum
Causticum
Chamomilla
Cimicifuga
Coffea cruda
Drosera
Eupatorium perf
Euphrasia
Ferrum phos
Gelsemium
Hamamelis
Hepar sulph calc
Hydrastis
Hypericum
Ignatia
Ipecac
Kali bic
Kali carb
Kali mur
Kali phos
Lachesis
Ledum
Lycopodium
Mag phos
Nat mur
Nux vom
Petroleum
Phosphoricum ac
Phytolacca
Podoph pelt
Pulsatilla
Rhus tox
Ruta
Sepia
Staphysag
Sulphur
Symphytum
Thuja occ

USES

To relieve symptoms of fear, hemorrhoids, head cold, warts, stings, bruises, vomiting, fever, bruised soreness, itching, worse motion, oberwork, cramps, hoarseness, irritability, minor back pain, sleeplessness, cough, flu-like symptoms, eye irritation, low fever, lethargy, varicose veins, croupiness, sinuses, shooting pain, sadness, nausea, sinuses, sour belching, congested ears, irritability, sore throat, black eyes, digestion, cramps, sneezing, vomiting, nausea, headache, sore throat, diarrhea, weeping, better motion, bruised feeling, indifference, anger, skin problems, prickling pain, and warts.

KEEP OUT OF REACH OF CHILDREN

Keep this and all medicines out of reach of children.

INDICATIONS

Acon nap fear

Aesculus hipp hemorrhoids

Allium cepa head cold

Antimon crud warts

Apis mel stings

Arnica bruises

Arsenicum alb vomiting

Belladonna fever

Bellis bruised soreness

Berber vulg itching

Bryonia worse motion

Calc carb overwork

Caulophyllum cramps

Causticum hoarseness

Chamomilla irritability

Cimicifuga minor back pain

Coffea cruda sleeplessness

Drosera cough

Eupatorium perf flu-like symptoms

Euphrasia eye irritation

Ferrum phos low fever

Gelsemium lethargy

Hamamelis varicose veins

Hepar sulph calc croupiness

Hydrastis sinuses

Hypericum shooting pain

Ignatia sadness

Ipecac nausea

Kali bic sinuses

Kali carb sour belching

Kali mur congested ears

Kali phos irritability

Lachesis sore throat

Ledum black eyes

Lycopodium digestion

Mag phos cramps

Nat mur sneezing

Nux vom vomiting

Petroleum nausea

Phosphoricum ac headache

Phytolacca sore throat

Podoph pelt diarrhea

Pulsatilla weeping

Rhus tox better motion

Ruta bruised feeling

Sepia indifference

Staphysag anger

Sulphur skin problems

Symphytum prickling pain

Thuja occ warts

STOP USE AND ASK DOCTOR

If symptoms persist/worsen or if pregnant or nursing, stop use and consult your practitioner.

DIRECTIONS

Adults: Dissolve 3 to 5 under the tongue three times a day or as directed by a licensed practitioner. Take at greater intervals as condition subsides.

Children: Dissolve 3 to 5 under the tongue three times a day or as directed by a licensed practitioner. Take at greater intervals as condition subsides.

INACTIVE INGREDIENTS

Sucrose/Lactose